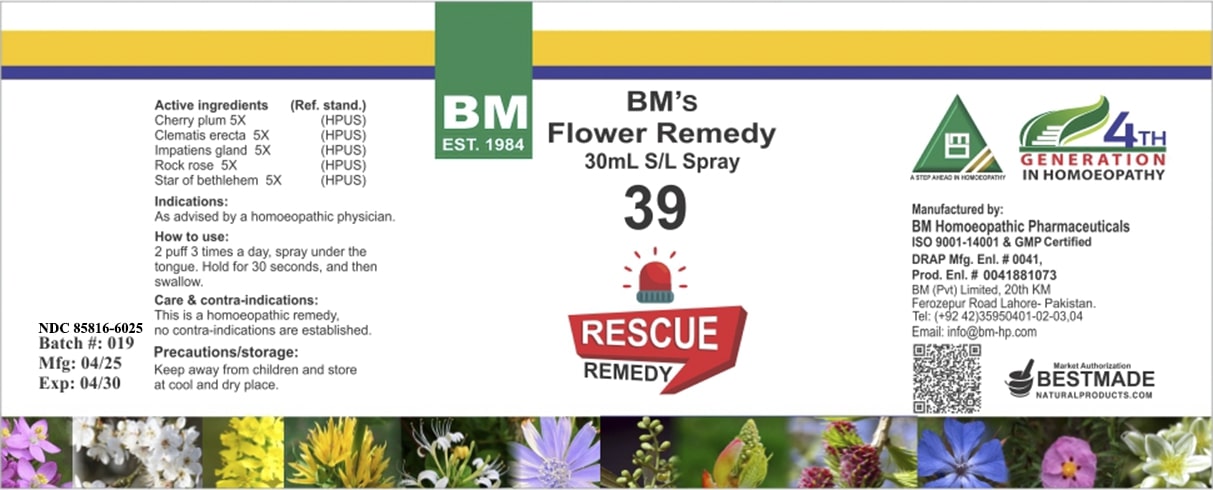 DRUG LABEL: BM Rescue Remedy (Instant Calm)
NDC: 85816-6025 | Form: SPRAY
Manufacturer: BM Private Limited
Category: homeopathic | Type: HUMAN OTC DRUG LABEL
Date: 20250627

ACTIVE INGREDIENTS: HELIANTHEMUM NUMMULARIUM FLOWER 5 [hp_X]/1 mL; CLEMATIS RECTA FLOWERING TOP 5 [hp_X]/1 mL; IMPATIENS GLANDULIFERA FLOWER 5 [hp_X]/1 mL; ORNITHOGALUM UMBELLATUM 5 [hp_X]/1 mL; PRUNUS CERASIFERA FLOWER 5 [hp_X]/1 mL
INACTIVE INGREDIENTS: GLYCERIN 0.001 mL/1 mL; ALCOHOL 0.3 mL/1 mL

BM Rescue Remedy (Instant Calm) spray

ACTIVE INGREDIENT

Active ingredients (Ref. stand.) Cherry plum 5X (HPUS) Clematis erecta 5X (HPUS) Impatiens gland 5X (HPUS) Rock rose 5X (HPUS) Star of bethlehem 5X (HPUS)

INACTIVE INGREDIENT

Ethanol 30%, Glycerin

PURPOSE

Indications: As advised by a homoeopathic physician.

Indications: As advised by a homoeopathic physician.

DOSAGE AND ADMINISTRATION

How to use: 2 puff 3 times a day, spray under the tongue. Hold for 30 seconds, and then swallow.

CONTRAINDICATIONS

Care & contra-indications: This is a homoeopathic remedy, no contra-indications are established.

WARNINGS

Precautions/storage: Keep away from children and store at cool and dry place.

KEEP OUT OF REACH OF CHILDREN

Precautions/storage: Keep away from children and store at cool and dry place.

STORAGE AND HANDLING

Precautions/storage: Keep away from children and store at cool and dry place.

Entire package label